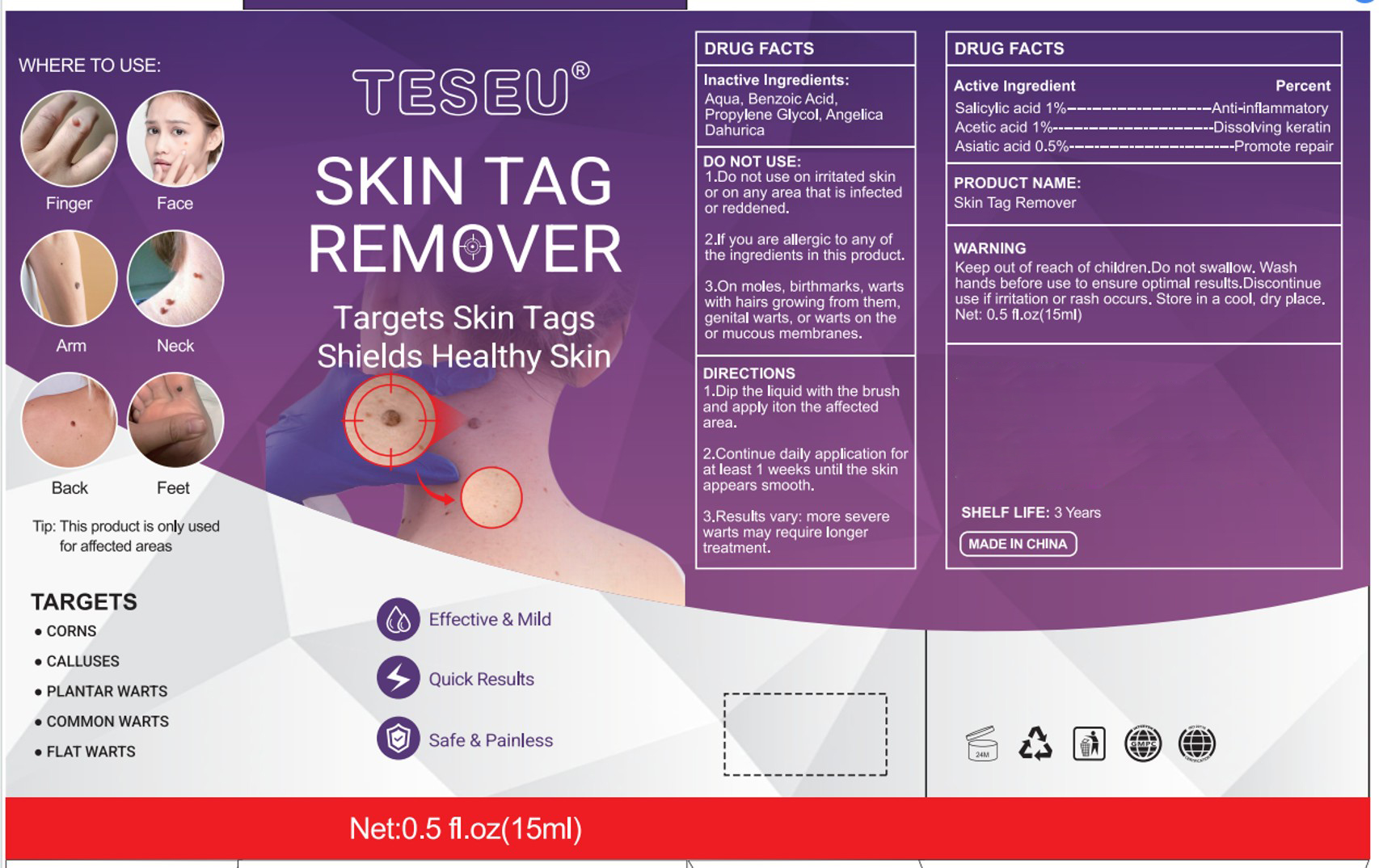 DRUG LABEL: SKIN TAG REMOVER
NDC: 87191-001 | Form: LIQUID
Manufacturer: Shenzhen Yaozhihong Technology Co., Ltd.
Category: otc | Type: HUMAN OTC DRUG LABEL
Date: 20251029

ACTIVE INGREDIENTS: SALICYLIC ACID 0.01 g/1 mL; ACETIC ACID 0.01 g/1 mL; ASIATIC ACID 0.005 g/1 mL
INACTIVE INGREDIENTS: PROPYLENE GLYCOL; ANGELICA DAHURICA SEED; AQUA; BENZOIC ACID

87191-001 SKIN TAG REMOVER

ACTIVE INGREDIENT

Salicylic acid 1%
ACETIC ACID 1%
ASIATIC ACID 0.5%

PURPOSE

Anti-inflammatory
Dissolving keratin
Promote repair

INDICATIONS AND USAGE

Targets Skin Tags Shields Healthy Skin

Keep out of reach of children.Do not swallow. Washhands before use to ensure optimal results.Discontinueuse if irritation or rash occurs, Store in a cool, dry place.Net: 0.5 f.oz(15ml)

DO NOT USE

1.Do not use on irritated skinor on any area that is infectedor reddened.
2.lf you are allergic to any ofthe ingredients in this product.
3.On moles, birthmarks, wartswith hairs growing from them,genital warts, or warts on theor mucous membranes.

Keep out of reach of children.
Do not swallow. Washhands before use to ensure optimal results.

STOP USE

Discontinueuse if irritation or rash occurs, Store in a cool, dry place.

Keep out of reach of children.

DOSAGE AND ADMINISTRATION

1.Dip the liquid with the brushand apply iton the affectedarea.
2.Continue daily application forat least 1 weeks until the skinappears smooth.
3.Results vary: more severewarts may require longertreatment.

INACTIVE INGREDIENT

AQUA
BENZOIC ACID
PROPYLENE GLYCOL
ANGELICA DAHURICA